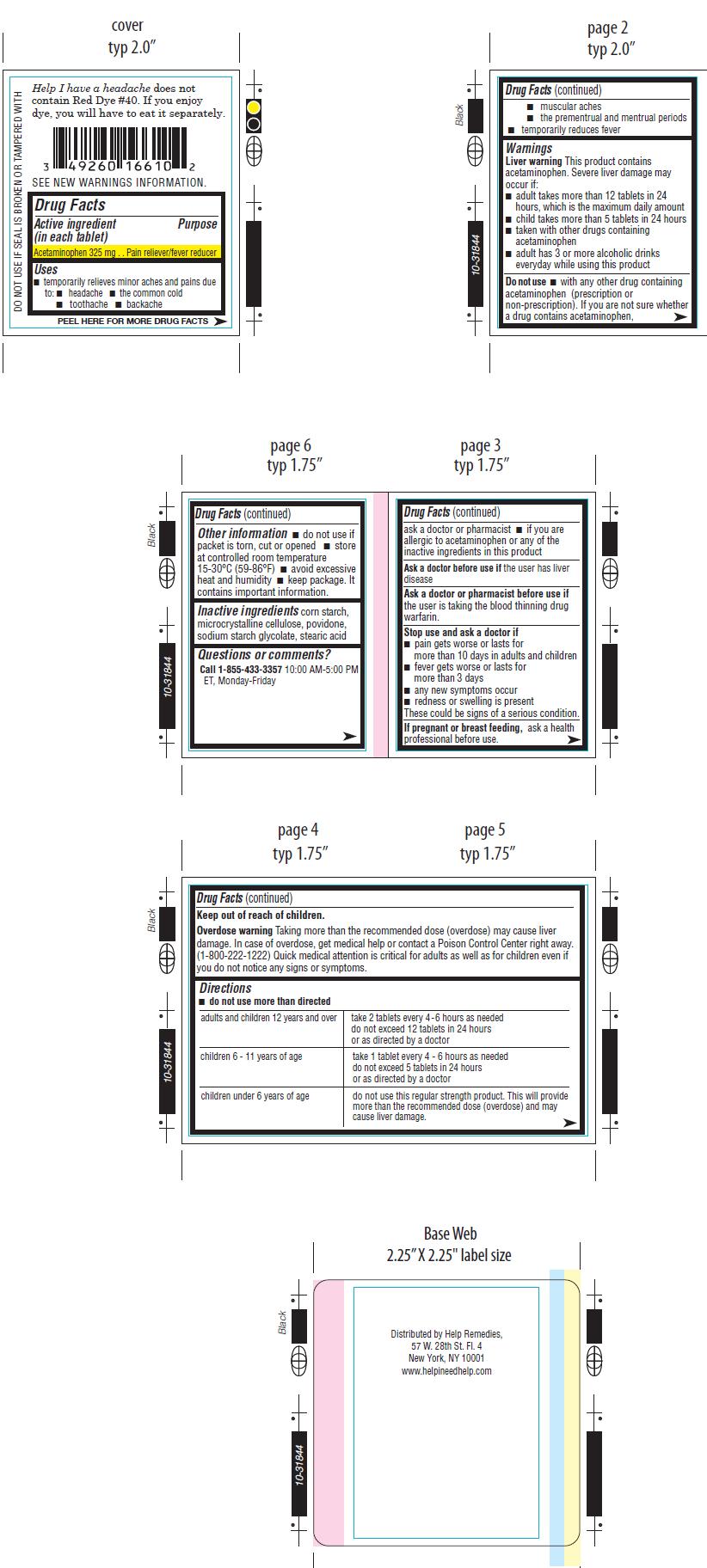 DRUG LABEL: Help I Have a Headache
NDC: 49260-710 | Form: TABLET
Manufacturer: Help Remedies, Inc.
Category: otc | Type: HUMAN OTC DRUG LABEL
Date: 20120709

ACTIVE INGREDIENTS: ACETAMINOPHEN 325 mg/1 1
INACTIVE INGREDIENTS: STARCH, CORN; CELLULOSE, MICROCRYSTALLINE; POVIDONE; SODIUM STARCH GLYCOLATE TYPE A POTATO; STEARIC ACID

Drug Facts

Active Ingredient................. Purpose
(in each tablet)
Acetaminophen 325mg.............Pain reliever/fever reducer

Uses:

• temporarily relieves minor aches and pains due to
• headache
• common cold
• toothache
• backache
• muscular aches
• premenstrual and menstrual cramps
• temporarily reduces fever

Warnings:
Liver warning This product contains acetaminophen. Severe liver damage may occur if you take
• more than 12 tablets in 24 hours,
which is the maximum daily amount.
• child takes more than 5 tablets in 24 hours
• taken with other drugs containing acetaminophen.
• adult has 3 or more alcoholic drinks everyday
while using this product.
Overdose warning Taking more than the recommended dose (overdose) may cause liver damage.
In case of overdose, get medical help or contact a Poison Control Center right away.
(1-800-222-1222) Quick medical attention is critical for adults as well as for children even if
you do not notice any signs or symptoms. Prompt medical attention is critical for
adults as well as for children even if you do not notice any signs or symptoms.

Do not use

• with any other drug containing acetaminophen (prescription or non-prescription) If you are not sure whether a drug contains acetaminophen, ask a doctor or pharmacist

• if you are allergic to acetaminophen or any of the inactive ingredients in this product

Ask a doctor before use if the user has liver disease.

Ask a doctor or pharmacist before use if the user is taking the blood thinning drug warfarin.

Stop use and ask a doctor if

• pain gets worse or lasts for more than 10 days in adults and childre

• fever gets worse or lasts for more than 3 days

• any new symptoms occur

• redness or swelling is present

These could be signs of a serious condition

Keep out of reach of children.

PREGNANCY OR BREAST FEEDING

If pregnant or breast feeding, ask a health professional before use.

Other Information
• do not use if packet is torn, cut or opened
• store at controlled room temperature 15-30 degrees celcius (59-86 degrees fahrenheits)
• avoid excessive heat and humidity
• keep package.It contains important information.

Directions
•do not take more than directed

adults and children 12 years and over | take 2 tablets every 4-6 hours as needed do not exceed 12 tablets in 24 hours or as directed by doctor
children 6-11 years of age | take 1 tablet every 4-6 hours as needed do not exceed 5 tablets in 24 hours or as directed by a doctor
children under 6 years of age | do not use this regular strength product. This will provide more than the recommended dose (overdose) and may cause liver damage.

INACTIVE INGREDIENT

Inactive Ingredients corn starch,microcrystalline cellulose, povidone, sodium
starch glycolate, stearic acid

Questions or comments?

Call 1-855-433-335710:00 AM - 5:00 PM ET, Monday-Friday